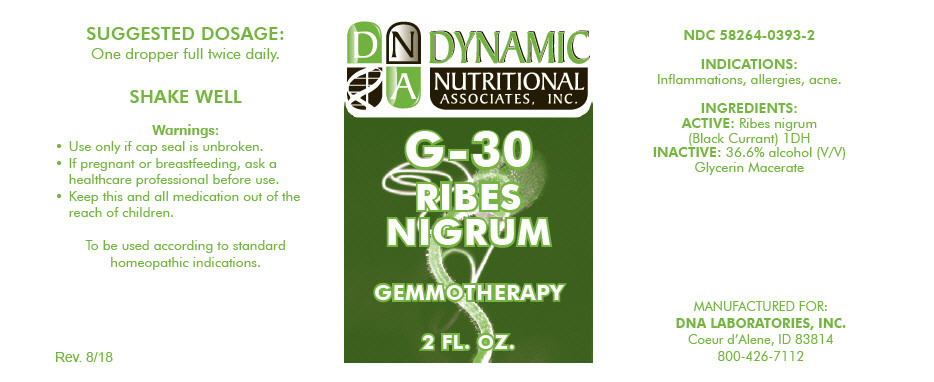 DRUG LABEL: G-30
NDC: 58264-0393 | Form: SOLUTION
Manufacturer: DNA Labs, Inc.
Category: homeopathic | Type: HUMAN OTC DRUG LABEL
Date: 20250129

ACTIVE INGREDIENTS: RIBES NIGRUM FLOWER BUD 1 [hp_X]/1 mL
INACTIVE INGREDIENTS: ALCOHOL; WATER

G-30

NDC 58264-0393-2

INDICATIONS AND USAGE

INDICATIONS

Inflammations, allergies, acne.

INGREDIENTS

ACTIVE

Ribes nigrum (Black Currant) 1DH

INACTIVE

36.6% alcohol (V/V) Glycerin Macerate

SUGGESTED DOSAGE

One dropper full twice daily.

STORAGE AND HANDLING

SHAKE WELL

Warnings

- Use only if cap seal is unbroken.

PREGNANCY OR BREAST FEEDING

- If pregnant or breastfeeding, ask a healthcare professional before use.

KEEP OUT OF REACH OF CHILDREN

- Keep this and all medication out of the reach of children.

To be used according to standard homeopathic indications.

PRINCIPAL DISPLAY PANEL - 2 FL. OZ. Bottle Label

DYNAMIC
NUTRITIONAL
ASSOCIATES, INC.

G-30

RIBES
NIGRUM

GEMMOTHERAPY

2 FL. OZ.